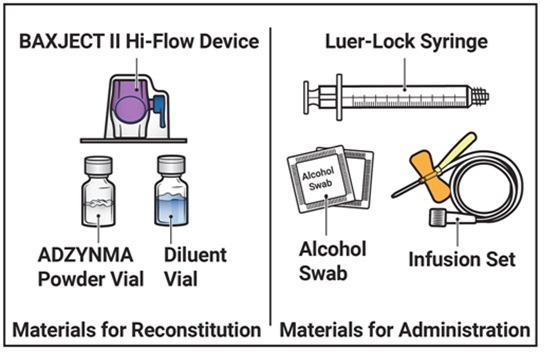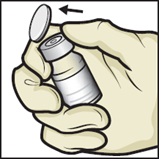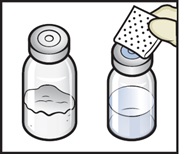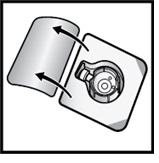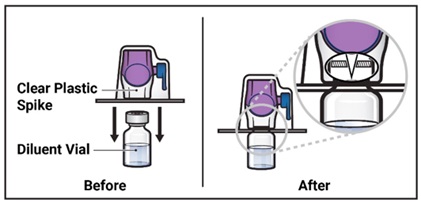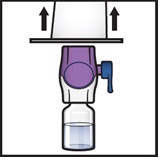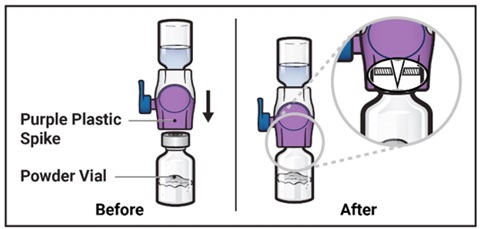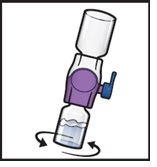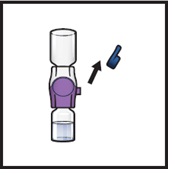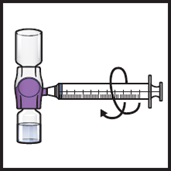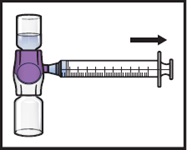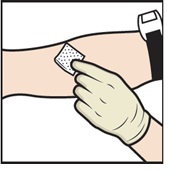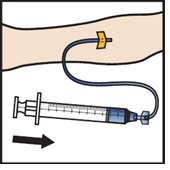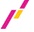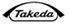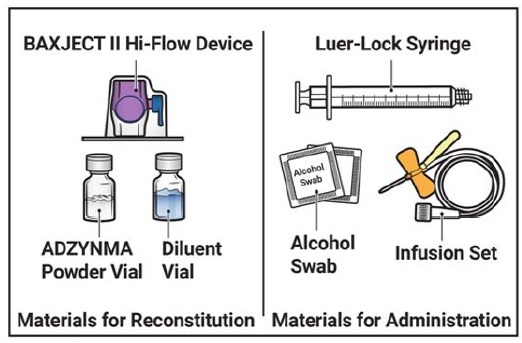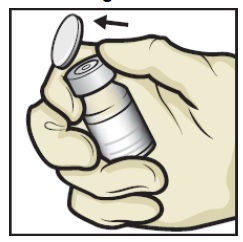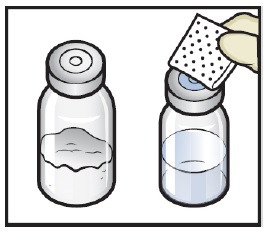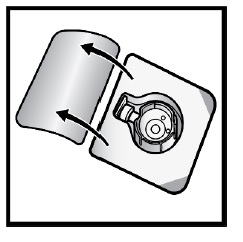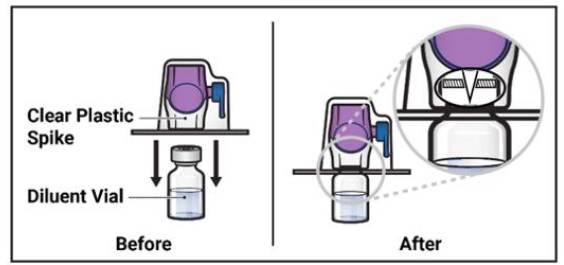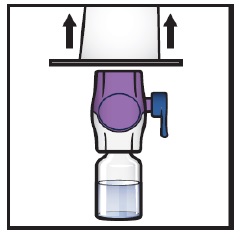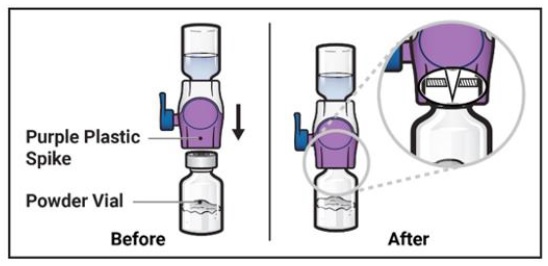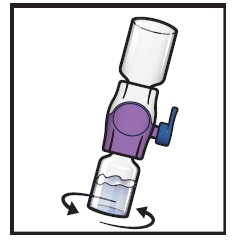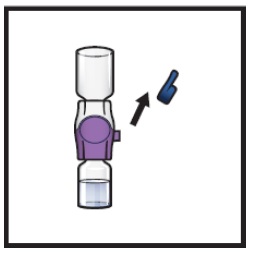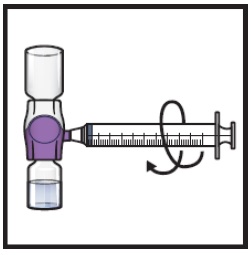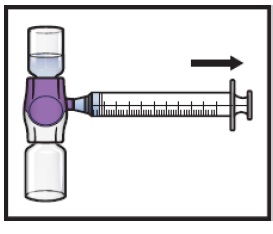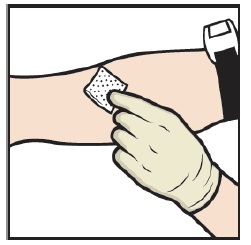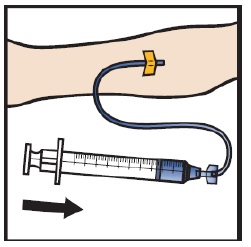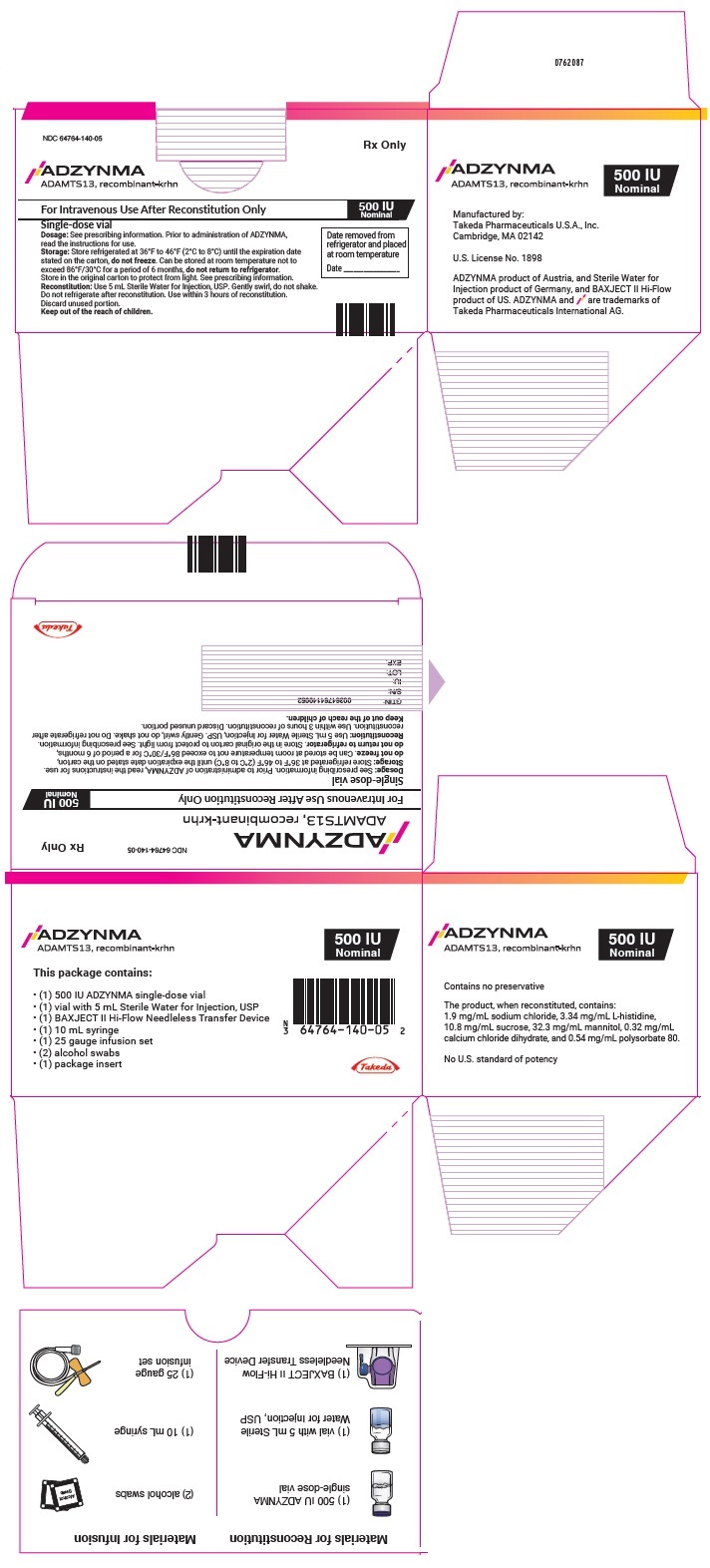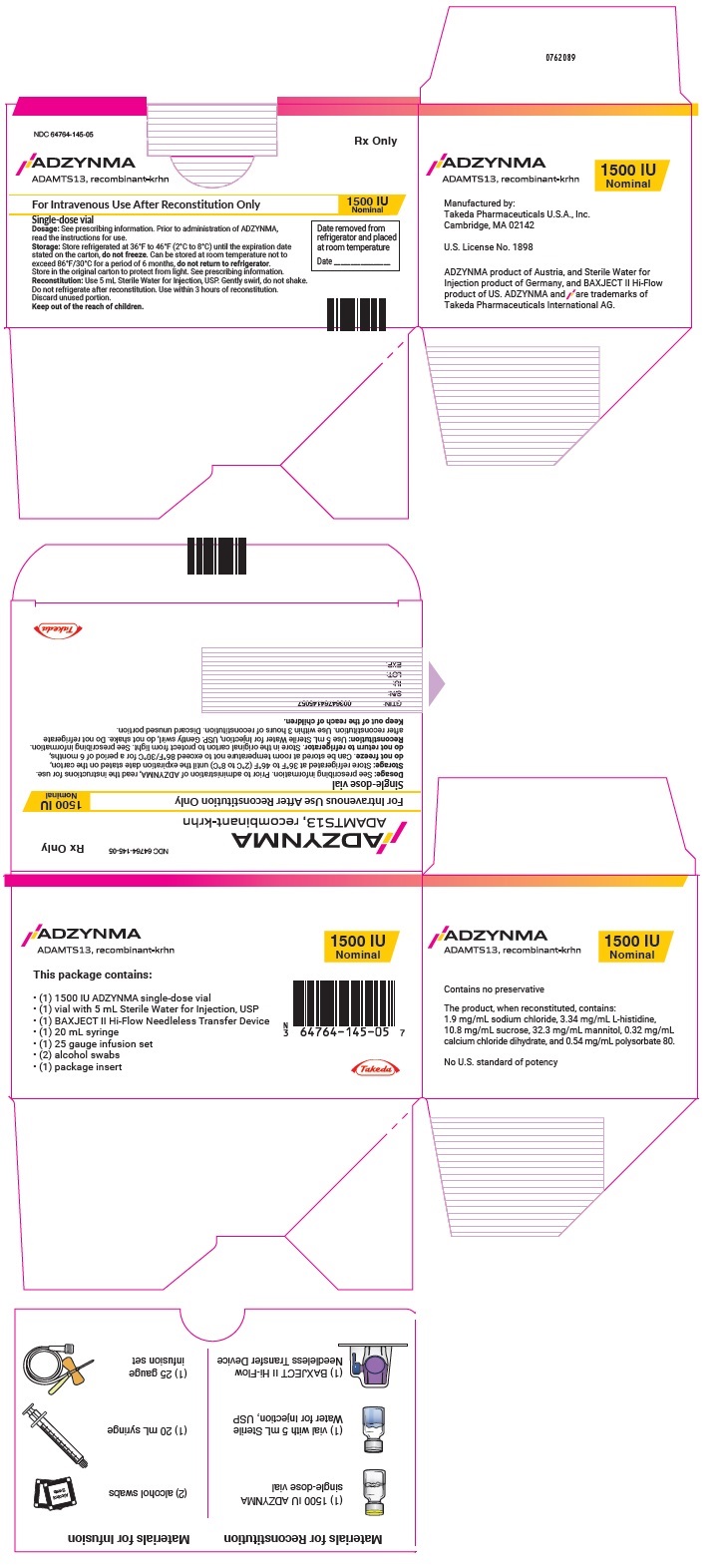 DRUG LABEL: ADZYNMA
NDC: 64764-140 | Form: KIT | Route: INTRAVENOUS
Manufacturer: TAKEDA PHARMACEUTICALS AMERICA, INC.
Category: prescription | Type: HUMAN PRESCRIPTION DRUG LABEL
Date: 20240830

ACTIVE INGREDIENTS: Apadamtase Alfa 500 [iU]/1 [iU]
INACTIVE INGREDIENTS: Sodium Chloride; Calcium Chloride; Histidine; Mannitol; Sucrose; Polysorbate 80; WATER 5 mL/5 mL

HIGHLIGHTS OF PRESCRIBING INFORMATION

These highlights do not include all the information needed to use ADZYNMA safely and effectively. See full prescribing information for ADZYNMA.
ADZYNMA (ADAMTS13, recombinant-krhn)
lyophilized powder for Injection, for intravenous use
Initial U.S. Approval: 2023

1 INDICATIONS AND USAGE

ADZYNMA (ADAMTS13, recombinant-krhn) is a human recombinant “A disintegrin and metalloproteinase with thrombospondin motifs 13” (rADAMTS13) indicated for prophylactic or on demand enzyme replacement therapy (ERT) in adult and pediatric patients with congenital thrombotic thrombocytopenic purpura (cTTP). (1)

2 DOSAGE AND ADMINISTRATION

For intravenous use after reconstitution only. (2)

Prophylactic Therapy

- Administer 40 IU/kg body weight once every other week intravenously at a rate of 2 to 4 mL per minute. (2.1)
- The prophylaxis dosing frequency may be adjusted to 40 IU/kg body weight once weekly based on prior prophylactic dosing regimen or clinical response. (2.1)

On-Demand Therapy

Administer intravenously at a rate of 2 to 4 mL per minute:

- 40 IU/kg body weight on day 1. (2.1)
- 20 IU/kg body weight on day 2. (2.1)
- 15 IU/kg body weight on day 3 and beyond until two days after the acute event is resolved. (2.1)

3 DOSAGE FORMS AND STRENGTHS

ADZYNMA is available as a lyophilized powder in single-dose vials containing nominally 500 or 1500 international units. (3)

4 CONTRAINDICATIONS

Do not use in patients who have manifested life threatening hypersensitivity reactions to ADZYNMA or its components. (4)

5 WARNINGS AND PRECAUTIONS

Hypersensitivity reactions may occur. Discontinue ADZYNMA if hypersensitivity symptoms occur and administer appropriate emergency treatment. (5.1)

Immunogenicity: Patients may develop antibodies to rADAMTS13 which could potentially result in a decreased or lack of response to rADAMTS13. Patients may develop antibodies to host cell proteins which could potentially result in adverse reactions. There are no data on risk in previously untreated patients (subjects naïve to plasma-based products). (5.2)

6 ADVERSE REACTIONS

Most common adverse reactions (incidence >5%) are headache, diarrhea, migraine, abdominal pain, nausea, upper respiratory tract infection, dizziness, and vomiting. (6.1)

To report SUSPECTED ADVERSE REACTIONS, contact Takeda Pharmaceuticals U.S.A., Inc. at 1-877-TAKEDA-7 (1-877-825-3327) or FDA at 1-800-FDA-1088 or www.fda.gov/medwatch.

FULL PRESCRIBING INFORMATION

1 INDICATIONS AND USAGE

ADZYNMA (ADAMTS13, recombinant-krhn) is a human recombinant “A disintegrin and metalloproteinase with thrombospondin motifs 13” (rADAMTS13) indicated for prophylactic or on demand enzyme replacement therapy (ERT) in adult and pediatric patients with congenital thrombotic thrombocytopenic purpura (cTTP) [see Use in Specific Populations (8.4), Clinical Studies (14)].

2 DOSAGE AND ADMINISTRATION

For intravenous use after reconstitution only.

2.1 Dosage

- Each vial of ADZYNMA is labeled with the actual rADAMTS13 activity, measured in terms of its potency in International Units (IU).
- Calculate administration dose and volume based on the patient's body weight using the actual potency (and not the nominal potency) as printed on ADZYNMA vial.
- For Intravenous (IV) Infusion at a rate of 2 to 4 mL per minute.

Prophylactic Therapy

The recommended prophylactic dosage regimen of ADZYNMA is as follows:

- Administer 40 IU/kg body weight once every other week.
- The prophylactic dosing frequency may be adjusted to 40 IU/kg body weight once weekly based on prior prophylactic dosing regimen or clinical response [see Use in Specific Populations (8.4), Clinical Pharmacology (12.3), Clinical Studies (14)].

On-Demand Therapy

A guide for dosing ADZYNMA for on demand treatment of an acute event is provided in Table 1.

Table 1: Dosing for On-Demand Therapy
Treatment Day 1 | Treatment Day 2 | Treatment Day 3 and Beyond
40 IU/kg | 20 IU/kg | 15 IU/kg once daily until two days after the acute event is resolved.

2.2 Preparation and Administration

- Use aseptic technique (clean and germ-free) throughout the procedure.
- Check the expiration date of the product prior to use.
- Do not use ADZYNMA if the expiration date has passed.

Reconstitution

1. Prepare a clean, germ-free, flat surface and gather all the materials you will need for the reconstitution and infusion. Figure A depicts the materials provided in the carton box.

Figure A

2. Do not use ADZYNMA if the expiration date has passed.
  - Use ADZYNMA within 3 hours after reconstitution and keep at room temperature not to exceed 86°F/30°C. Do not store at any other temperature. Discard any unused reconstituted product if not used within 3 hours after reconstitution.
3. Allow the vials of ADZYNMA and diluent to reach room temperature before use.
  - If the patient needs more than one vial of ADZYNMA per injection, reconstitute each vial according to the instructions stated under ‘Reconstitution’.
  - Inspect the reconstituted ADZYNMA solution for particulate matter and discoloration prior to administration. The solution should be clear and colorless in appearance.
  - Do not administer if particulate matter or discoloration is observed.
4. Wash and dry your hands thoroughly, and put on clean exam gloves.
5. Remove plastic caps from the ADZYNMA and diluent vials and place the vials on a flat surface (Figure B).

Figure B

6. Wipe the rubber stoppers with an alcohol swab and allow them to dry prior to use (Figure C).

Figure C

7. Open the BAXJECT II Hi-Flow device package by peeling away the lid, without touching the inside (Figure D).
  - Do not remove the BAXJECT II Hi-Flow device from the package.
  - Do not touch the clear plastic spike.

Figure D

8. Turn the package with the BAXJECT II Hi-Flow device upside down and place it over the top of the diluent vial. Press straight down until the clear plastic spike pierces through the diluent vial stopper (Figure E).

Figure E

9. Grip the BAXJECT II Hi-Flow device package at its edge and pull the package off the device (Figure F).
  - Do not remove the blue cap from the BAXJECT II Hi-Flow device.
  - Do not touch the exposed purple plastic spike.

Figure F

10. Turn the system over so that the diluent vial is now on top. Press the BAXJECT II Hi-Flow device straight down until the purple plastic spike pierces through the ADZYNMA powder vial stopper (Figure G). The vacuum will draw the diluent into the ADZYNMA powder vial.
  - You may notice some bubbles or foam – this is normal and should soon disappear. Wait until foam or bubbles dissipate before administration.

Figure G

11. Swirl the connected vials gently and continuously until the powder is completely dissolved (Figure H).
  - Do not shake the vial.

Figure H

12. Visually inspect the reconstituted solution for particulate matter before administration. The solution should be clear and colorless in appearance.
  - Do not use the product if particulate matter or discoloration is observed.
13. If the dose requires more than one vial of ADZYNMA, repeat step 1 to step 12 to reconstitute each vial.
  - Use a different BAXJECT II Hi-Flow device to reconstitute each vial of ADZYNMA and diluent.

Administration Instructions

14. Take off the blue cap from the BAXJECT II Hi-Flow device (Figure I). Attach a Luer-lock syringe (Figure J).
  - Do not inject air into the system.

Figure I

Figure J

15. Turn the system upside down (ADZYNMA vial is now on top). Draw the reconstituted solution into the syringe by pulling the plunger back slowly (Figure K).
  - Use ADZYNMA within 3 hours after reconstitution and keep at room temperature not to exceed 86°F/30°C. Do not store at any other temperature. Discard any unused reconstituted product if not used within 3 hours after reconstitution.
  - Do not administer ADZYNMA in the same tubing or container at the same time with other medicinal products for infusion.

Figure K

16. If a patient is to receive more than one vial of ADZYNMA, the contents of multiple vials can be drawn into the same syringe. Repeat this process for all reconstituted vials of ADZYNMA until the total volume to be administered is reached.
17. Disconnect the syringe and attach a suitable injection needle or an infusion set.
18. Point the needle up and remove any air bubbles by gently tapping the syringe with your finger and slowly and carefully pushing air out of the syringe and needle.
19. Apply a tourniquet and clean the chosen infusion site with an alcohol swab (Figure L).

Figure L

20. Insert the needle into the vein and remove the tourniquet.
21. Infuse the reconstituted ADZYNMA slowly, at a rate of 2 to 4 mL per minute (Figure M).
  - A syringe pump may be used to control the rate of administration.

Figure M

22. Take the needle out of the vein, place a cotton ball or gauze on the infusion site, and apply pressure for several minutes to stop bleeding.
  - Do not recap the needle.
23. Place the needle, syringe, and empty vials in a puncture-resistant sharps container.
  - Do not dispose of syringes and needles in the regular waste.

3 DOSAGE FORMS AND STRENGTHS

ADZYNMA is a lyophilized powder in single-dose vials containing nominally 500 or 1500 International Units (IU) per vial and comes with 5 mL of Sterile Water for Injection. Each carton and vial label for ADZYNMA states the actual potency of ADAMTS13 in IU.

4 CONTRAINDICATIONS

ADZYNMA is contraindicated in patients who have manifested life threatening hypersensitivity reactions to ADZYNMA or its components [see Description (11)].

5 WARNINGS AND PRECAUTIONS

5.1 Hypersensitivity

Allergic-type hypersensitivity including anaphylactic reactions may occur with ADZYNMA. Patients should be informed of the early signs of hypersensitivity including but not limited to tachycardia, tightness of the chest, wheezing and/or acute respiratory distress, hypotension, generalized urticaria, pruritus, rhinoconjunctivitis, angioedema, lethargy, nausea, vomiting, paresthesia, and restlessness. If signs and symptoms of severe allergic reactions occur, immediately discontinue administration of ADZYNMA and provide appropriate supportive care.

5.2 Immunogenicity

There is a potential for immunogenicity with ADZYNMA. Patients may develop neutralizing antibodies to ADAMTS13, which could potentially result in a decreased or lack of response to ADAMTS13. Neutralizing antibodies were not reported in the cTTP clinical trials. All subjects had been previously exposed to ADAMTS13 through plasma-based products. There are no data on immunogenicity with ADZYNMA in previously untreated patients (subjects naïve to plasma-based products) [see Clinical Pharmacology (12.6)].

Patients may develop antibodies to host cell proteins which could potentially result in adverse reactions. There are no data on immunogenicity to host cell proteins in previously untreated patients (subjects naïve to plasma-based products).

6 ADVERSE REACTIONS

Most common adverse reactions (>5% of subjects) reported in clinical trials were headache, diarrhea, migraine, abdominal pain, nausea, upper respiratory tract infection, dizziness, and vomiting.

6.1 Clinical Trials Experience

Because clinical trials are conducted under widely varying conditions, adverse reaction rates observed in the clinical trials of a drug cannot be directly compared to rates in the clinical trials of another drug and may not reflect the rates observed in practice.

The safety profile of ADZYNMA was evaluated in one, prospective, randomized, active-controlled, open-label, multicenter, two-period crossover study (Study 1). The adverse drug reactions (ADR) are listed in Table 2.

Table 2: Adverse Reactions Reported in >5% of Patients Treated with ADZYNMA
Adverse Reaction | ADZYNMA (N= 48) n (%) [Percentages by patient were calculated using the number of all subjects who had the listed adverse event.]
Headache | 15 (31.3)
Diarrhea | 8 (16.7)
Migraine | 7 (14.6)
Abdominal pain | 6 (12.5)
Nausea | 6 (12.5)
Upper respiratory tract infection | 6 (12.5)
Dizziness | 5 (10.4)
Vomiting | 5 (10.4)
N = Total number of patients treated with ADZYNMA in Study 1.
n = Number of patients who had at least one event in the category.

8 USE IN SPECIFIC POPULATIONS

8.1 Pregnancy

Risk Summary

The safety of ADZYNMA for use during pregnancy has not been established in controlled clinical trials. Limited data with ADZYNMA use during pregnancy are insufficient to inform a drug-associated risk of adverse developmental outcomes.^1 In determining whether ADZYNMA should be used in pregnancy, healthcare providers should balance the potential benefits with the potential risks.

The background rate of major birth defects and miscarriage in the indicated population is unknown. In the U.S. general population, the estimated background rate of major birth defects and miscarriage in clinically recognized pregnancies is 2% to 4% and 15% to 20%, respectively.

Data

Human Data

There have been four cTTP patients exposed to ADZYNMA during pregnancy.

Two patients in a long-term extension study were found to be pregnant early in the first trimester while receiving prophylaxis with ADZYNMA. Both patients were discontinued from the study to comply with the protocol requirements. The first patient had no further exposure to ADZYNMA and had a first trimester miscarriage approximately two months after study discontinuation. The investigator assessed the event was unrelated to ADZYNMA. The second patient resumed treatment with ADZYNMA under a compassionate use program and delivered a healthy full-term baby with no safety concerns reported by the investigator.

Two additional cTTP patients were treated with ADZYNMA in a compassionate use program during pregnancy. The first patient, in the third trimester of her second pregnancy, experienced a stroke and thrombocytopenia that was refractory to daily plasmapheresis. At 33 weeks of gestation, ADZYNMA treatment was started once weekly. ADAMTS13 activity levels normalized, thrombocytopenia resolved, and a healthy baby was delivered at 37 weeks with no safety concerns reported by the treating physician due to ADZYNMA.^1 The second patient had an exacerbation of her cTTP during her second trimester of pregnancy despite prior daily plasma exchange. Her pregnancy was considered to be at risk, with inadequate response to plasma-based therapies. ADZYNMA was started once weekly and induced clinical remission. The baby was delivered by a cesarean section at week 29 and the treating physician reported no adverse events due to ADZYNMA.

Whether ADZYNMA should be used in pregnancy is solely up to the medical judgment of the healthcare provider.

Nonclinical Data

In an embryo-fetal development study in rats, ADZYNMA was administered in female rats at 80, 200, or 400 IU/kg [up to 10x human equivalent dose (HED)] every third day from 2 weeks before mating through Day 16 of gestation and was not associated with any adverse maternal findings or treatment-related effects on embryo-fetal development. In a pre- and post-natal development study in rats, ADZYNMA was administered at 80, 200, or 400 IU/kg [up to 10x HED] by intravenous (IV) bolus injection every three days from Day 6 of gestation to weaning at approximately Day 21 of lactation. There were no adverse maternal effects or findings in F1 or F2 offspring.

8.2 Lactation

Risk Summary

There is no information regarding the presence of ADZYNMA in human milk, its effects on milk production or the breastfed infant. The developmental and health benefits of breastfeeding should be considered along with the mother’s clinical need for ADZYNMA and any potential adverse effects to the breastfed child.

8.4 Pediatric Use

The safety and effectiveness of ADZYNMA has been established in pediatric patients. Clinical trials included patients aged 2 years and older. Based on data from population pharmacokinetic (PK) analysis, no additional dose adjustments beyond body weight are required for this age group. The recommended body-weight based dosing regimen in pediatric patients is the same as that in adults.

8.5 Geriatric Use

Clinical studies of ADZYNMA did not include patients 65 years of age and older to determine whether they respond differently from younger patients. Based on the results from population pharmacokinetics analysis, no dose adjustment is required for elderly patients [see Clinical Pharmacology (12.3)].

11 DESCRIPTION

ADZYNMA is a purified bivariant human recombinant “A disintegrin and metalloproteinase with thrombospondin motifs 13” (rADAMTS13) expressed in Chinese Hamster Ovary (CHO) cells using recombinant DNA technology (a mixture of Native rADAMTS13 Q23 and Variant rADAMTS13 R23 with a controlled range of the two variants ratio). ADZYNMA is produced and formulated without the addition of any exogenous raw materials of human or animal origin in the cell culture, purification, or formulation of the final product. The purification process for rADAMTS13 does not include use of a monoclonal antibody reagent. To enhance viral safety, the production process also incorporates two dedicated viral clearance steps – a solvent/detergent treatment step for inactivation and a 20 nm filtration step for removal of viruses. Recombinant ADAMTS13 has a molecular weight of approximately 172 kDa. Proteins that may be present in the final product, other than rADAMTS13, are trace quantities of host cell (CHO) proteins.

ADZYNMA (rADAMTS13) is a sterile, nonpyrogenic, preservative free, white powder supplied in single-dose vials for IV use after reconstitution. Each single-dose vial contains nominally 500 IU or 1500 IU of rADAMTS13, sodium chloride (9.4 mg), calcium chloride dihydrate (1.6 mg), L-histidine (16.7 mg), mannitol (161.4 mg), sucrose (53.8 mg), and polysorbate 80 (2.7 mg). Each vial of ADZYNMA is labeled with the specific number of units of ADAMTS13 potency expressed in IU as measured with a fluorescence resonance energy transfer (FRET) assay using a synthetic 73-amino-acid peptide (FRETS-VWF73). The potency assignment employs an ADAMTS13 concentrate standard that is referenced to a WHO (World Health Organization) international standard for ADAMTS13 concentrates and is evaluated by appropriate methodology to ensure accuracy of the results.

After reconstitution with 5 mL of Sterile Water for Injection, USP, the 500 IU and the 1500 IU vials result in a nominal potency of 100 IU/mL and 300 IU/mL, respectively. All dosage strengths yield a clear, colorless solution, free from particles with a pH of approximately 7.0.

12 CLINICAL PHARMACOLOGY

12.1 Mechanism of Action

ADZYNMA is a recombinant form of the endogenous ADAMTS13. ADAMTS13 is a plasma zinc metalloprotease that regulates the activity of von Willebrand factor (VWF) by cleaving large and ultra-large VWF multimers to smaller units and thereby reducing the platelet binding properties of VWF and its propensity to form microthrombi.^2,^3

12.2 Pharmacodynamics

VWF antigen (VWF:AG) and VWF:ristocetin cofactor activity (VWF:RCo) were used to assess VWF platelet binding activity. Following IV doses of ADZYNMA at the recommended dose, both VWF:AG and VWF:RCo transiently decreased for 1 to 2 days with a 15% to 25% change from baseline.

12.3 Pharmacokinetics

The PK profile of ADZYNMA was determined based on clinical trial ADAMTS13 activity data analyses.

Following single-dose IV administration of ADZYNMA at 5 IU/kg, 20 IU/kg, and 40 IU/kg to adults and adolescents, dose-related increases in individual ADAMTS13 activity were observed and reached a maximum at approximately 1-hour post-infusion or earlier. At a dose of 40 IU/kg the mean (SD) half-life and mean residence time (MRT) in adults and adolescents were 47.8 (13.7) hours and 63.8 (16.0) hours, respectively.

The PK parameters of ADAMTS13 activity following IV administration of ADZYNMA at 40 IU/kg in adults and adolescents are described in Table 3.

Table 3: Pharmacokinetic Parameters of ADAMTS13 Activity following IV Administration of ADZYNMA in cTTP Patients ≥12 Years Old
Parameter (unit) | Mean (SD) Min; Max (N=23)
Cmax (IU/mL) | 1.15 (0.25) 0.78; 1.56
IR [(IU/mL)/(IU/kg)] | 0.03 (0.01) 0.02; 0.04
t½ (h) | 47.8 (13.70) 30.1; 90.8
AUC0-inf (IUxh/mL) | 57.6 (13.9) 37.0; 88.2
AUC(0-168 h) (IUxh/mL) | 57.2 (13.67) 36.2; 87.2
MRT0-inf [N=22] (h) | 63.8 (16.0) 44.8; 113
Cave (0-168 h) (IU/mL) | 0.30 (0.07) 0.20; 0.46
Duration ADAMTS13 Activity above 10% (days) | 5.8 (1.2) 4.5; 8.9
AUC = area under ADAMTS13 activity-time curve; Cave (0-168 h) = average ADAMTS13 activity from 0 to 168 hours dosing interval; Cmax = maximum ADAMTS13 activity; IR = incremental recovery; MRT = mean residence time; t1/2 = half-life.
Note: 1 IU/mL ADAMTS13 activity corresponds to 100% average normal activity.

ADZYNMA IV administration at 40 IU/kg resulted in approximately 4- to 5-fold higher ADAMTS13 activity exposures (Cmax, AUC) and lower inter-subject variability when compared to plasma-based therapies. Mean time duration above 10% ADAMTS13 activity and mean average ADAMTS13 activity (Cave) were both approximately 3- to 4-fold higher following ADZYNMA IV administration than plasma-based therapies.

Based on Population PK analysis leveraging available data (N=65) from adults, adolescents and pediatric patients below 12 years of age, the mean (SD) steady state Cmax, AUCall, Cave, and duration of ADAMTS13 activity above 10% following IV administration of ADZYNMA every other week in cTTP patients below 12 years of age were 1.02 (0.19) IU/mL, 54.0 (12.2) IU*h/mL, 0.16 (0.04) IU/mL, and 6.8 (2.1) days, respectively.

ADAMTS13 antigen and activity PK characteristics (MRT, Vss, and CL) were similar across age groups in patients with cTTP. Body-weight based ADZYNMA dosing provides similar ADAMTS13 activity PK parameters (Cmax and Cave) across the different age groups including pediatric patients <12 years of age.

Specific Populations

Besides body-weight dosing regimen, no dose adjustment is required since no intrinsic factors such as age, gender, race, baseline estimated glomerular filtration rate (eGFR), and baseline bilirubin were identified as covariates impacting ADAMTS13 PK.

Pediatric Patients

Population pharmacokinetics (PK) analysis leveraging available data from adults, adolescents and pediatric patients below 12 years of age (N=65), suggests comparable ADAMTS13 activity exposures between patients below 12 years of age and patients aged 12 years and above receiving the recommended ADZYNMA dosing regimen [see Use in Specific Populations (8.4)].

12.6 Immunogenicity

The observed incidence of anti-drug antibodies (ADA) is highly dependent on the sensitivity and specificity of the assay. Differences in assay methods preclude meaningful comparisons of the incidence of ADA in the studies described below with the incidence of ADA in other studies, including those of ADZYNMA.

Thirteen (one patient in Study 1 and twelve patients in a long-term extension study) of 67 patients treated prophylactically with ADZYNMA with confirmed cTTP tested positive for low-titer binding antibodies against ADAMTS13 with no observable clinical impact on the safety or efficacy of ADZYNMA, and no increase in antibody titers over time. No cTTP patients tested positive for neutralizing antibodies against ADAMTS13.

Because of the low occurrence of ADA, the effect of these antibodies on the PK, PD, safety, and/or efficacy of rADAMTS13 products is unknown [see Warnings and Precautions (5.2)].

There are no data on immunogenicity in previously untreated patients (subjects naïve to plasma-based products), therefore, the risk of immunogenicity for naïve subjects to this drug product is unknown.

13 NONCLINICAL TOXICOLOGY

13.1 Carcinogenesis, Mutagenesis, Impairment of Fertility

No carcinogenicity or mutagenicity studies have been conducted with ADZYNMA to assess its mutagenic or carcinogenic potential.

No adverse effects on fertility were observed in female rats administered 80, 200, or 400 IU/kg ADZYNMA every third day for 2 weeks before mating through Day 16.

14 CLINICAL STUDIES

ADZYNMA was studied in a global, prospective, randomized, active-controlled, open-label, multicenter, two-period crossover study followed by a single arm continuation period (Study 1) evaluating the efficacy and safety of the prophylactic and on demand ERT with ADZYNMA compared to plasma-based therapies in patients with cTTP.

Prophylactic Enzyme Replacement Therapy in patients with cTTP

The efficacy of ADZYNMA in the prophylactic treatment of patients with cTTP was evaluated in Study 1, in 46 patients who were randomized to receive 6 months of treatment with either 40 IU/kg of ADZYNMA or plasma-based therapies (Period 1), then crossed over to the other treatment for 6 months (Period 2). Thirty-five patients have entered the 6-month single arm period with ADZYNMA (Period 3).

The median (min-max) age of patients was 32.5 years (range 3-58 years), with a mean weight of 67.6 kg. Most patients were white (65.2%), not Hispanic or Latino (80.4%) and were female (58.7%). Twenty of the 27 female patients (74.1%) were of child-bearing potential. Baseline characteristics are listed in Table 4.

Table 4: Baseline Characteristics of the Prophylactic Cohort
Characteristic | Prophylactic Cohort [The prophylactic cohort includes the patients who were originally enrolled in the prophylaxis cohort and the patients who moved to the prophylaxis cohort from the on demand cohort.] (N=46)
cTTP Pre-Study Treatment | 45 (97.8)
Fresh Frozen Plasma (FFP) [n (%)] | 32 (69.6)
Solvent/Detergent Treated Plasma [n (%)] | 10 (21.7)
FVIII-VWF Concentrations [n (%)] | 3 (6.5)
Acute TTP Events (in the 12 Months prior to screening) [n (%)] [Acute TTP events were defined in protocol by a drop in platelet count (≥50% of baseline or a platelet count <100,000/μL) and an elevation of lactate dehydrogenase (LDH) (>2 ×baseline or >2 ×upper limit normal (ULN)).]
Yes | 8 (17.4)
No | 38 (82.6)

The efficacy of prophylactic treatment with ADZYNMA in patients with cTTP was demonstrated based on the incidence of protocol defined acute and subacute TTP events and TTP manifestations (see Table 5), as well as the incidence of supplemental doses prompted by subacute TTP events over a 6-month time period.

No patients receiving ADZYNMA had an acute TTP event throughout the study, including Period 3 (with a median duration of exposure to ADZYNMA of 14 months for patients 12 to <18 years of age and patients ≥18 years of age; and 4 and 1 months in patients 6 to <12 and <6 years of age, respectively). One acute TTP event occurred in a patient receiving plasma-based therapies (FFP) prophylactically during Period 1 (see Table 5).

No subacute TTP events were reported in patients receiving ADZYNMA during Periods 1 and 2. In Period 3, two patients receiving ADZYNMA prophylaxis had two subacute events of which one was treated with four supplemental doses, 2 of FFP and 2 of ADZYNMA. Four patients receiving plasma-based therapies had five subacute TTP events in Periods 1 and 2. A total of seven supplemental doses, 2 of FVIII-VWF concentrate, 1 of FFP and 4 of ADZYNMA were given to three of these patients (see Table 5).

Table 5: Prophylactic Cohort Efficacy Results in cTTP Patients ≥12 Years of Age (Periods 1 and 2)
 | ADZYNMA N=37 | Plasma-Based Therapies N=38
Acute TTP events [Acute TTP events were defined by a drop in platelet count (≥50% of baseline or a platelet count <100,000/μL) and an elevation of lactate dehydrogenase (LDH) (>2× baseline or >2×upper limit normal (ULN)).]
Number of subjects with event (number of events) | 0 (0) | 1 (1)
Mean annualized event rate (SD) [Annualized event rate for a subject = number of events/duration of the observation period (years). Data shown are non-model based.] | 0 (0.000) | 0.05 (0.304)
Subacute TTP events [Subacute events were defined by a thrombocytopenia event or a microangiopathic hemolytic anemia event; and organ-specific signs and symptoms including but not limited to renal dysfunction events, neurological symptoms events, fever, fatigue/lethargy, and/or abdominal pain.]
Number of subjects with event (number of events) | 0 (0) | 4 (5)
Mean annualized event rate (SD) | 0 (0.000) | 0.27 (0.836)
TTP manifestations [TTP manifestations not shown also included renal dysfunction, neurological symptoms and abdominal pain. The clinical significance of the observed difference for the presented manifestations is unknown.]
Thrombocytopenia events [Thrombocytopenia events were defined as a drop in platelet count ≥25% of baseline or a platelet count <150,000/μL.]
Number of subjects with event (number of events) | 9 (30) | 19 (75)
Mean annualized event rate (SD) | 2.0 (4.706) | 4.44 (6.312)
Microangiopathic hemolytic anemia events [Microangiopathic hemolytic anemia events were defined as an elevation of LDH >1.5 ×baseline or >1.5 xULN.]
Number of subjects event (number of events) | 5 (7) | 11 (20)
Mean annualized event rate (SD) | 0.38 (1.028) | 1.47 (3.274)
SD = standard deviation; TTP = thrombotic thrombocytopenic purpura.

Overall, the efficacy results for ADZYNMA were consistent throughout the study, including Period 3 and across age groups. For outcome of ADZYNMA use in pregnancy [see Use in Specific Populations (8.1)].

On-Demand Enzyme Replacement Therapy

The efficacy of the on-demand (OD) enzyme replacement therapy was evaluated based on the proportion of acute TTP events responding to ADZYNMA in both the Prophylactic and the OD cohorts throughout the duration of the study.

An acute TTP event responding to ADZYNMA was defined as a resolved TTP event when platelet count was ≥150,000/μL or platelet count was within 25% of baseline, whichever occurs first, and LDH ≤1.5 x baseline or ≤1.5 x ULN, without requiring the use of another ADAMTS13-containing agent.

Five adult patients (≥18 years of age) enrolled in the OD cohort and had a total of six acute TTP events. Of these five patients, two patients were randomized to receive on-demand treatment with ADZYNMA and three patients were randomized to receive plasma-based therapies. All 6 acute TTP events resolved after treatment with either ADZYNMA or plasma-based therapies.

15 REFERENCES

1. Asmis, L. M., Serra, A., Krafft, A., Licht, A., Leisinger, E., Henschkowski-Serra, J., et al. 2022. Recombinant ADAMTS13 for Hereditary Thrombotic Thrombocytopenic Purpura. N Engl J Med, 387, 2356-2361.
2. Alwan, F., C. Vendramin, R. Liesner, A. Clark, W. Lester, T. Dutt, W. Thomas, R. Gooding, T. Biss, H. G. Watson, N. Cooper, R. Rayment, T. Cranfield, J. J. van Veen, Q. A. Hill, S. Davis, J. Motwani, N. Bhatnagar, N. Priddee, M. David, M. P. Crowley, J. Alamelu, H. Lyall, J. P. Westwood, M. Thomas and M. Scully (2019). “Characterization and treatment of congenital thrombotic thrombocytopenic purpura.” Blood 133(15): 1644-1651.
3. Sukumar, S., B. Lämmle and S. R. Cataland (2021). “Thrombotic Thrombocytopenic Purpura: Pathophysiology, Diagnosis, and Management.” J Clin Med 10(3): 536.

16 HOW SUPPLIED/STORAGE AND HANDLING

How Supplied

ADZYNMA (rADAMTS13) is a sterile, nonpyrogenic, preservative free, white powder supplied in single-dose vials packaged with:

- one vial with 5 mL sterile water for injection, USP
- one BAXJECT II Hi-FLOW needleless transfer device
- one syringe
- one 25 gauge infusion set
- two individually packaged alcohol swabs
- one package insert

ADZYNMA (rADAMTS13) is available in the following strengths:

Color Code | Nominal rADAMTS13 Potency | rADAMTS13 vial NDC | Carton NDC | Syringe Fill Size
Eggplant | 500 IU | 64764-130-01 | 64764-140-05 | 10 mL
Marigold | 1500 IU | 64764-135-01 | 64764-145-05 | 20 mL

The actual ADAMTS13 potency in international units is printed on the label of each ADZYNMA vial and carton.

Components are not made with natural rubber latex.

Storage and Handling

- Store at refrigerated temperature 2°C to 8°C (36°F to 46°F) for up to 36 months from the date of manufacture until expiration date stated on the ADZYNMA vial label and carton. Within this period, ADZYNMA may be stored at room temperature not to exceed 30°C/86°F for a period up to 6 months. After storage at room temperature, do not return to the refrigerator.
- Do not use beyond the expiration date printed on the ADZYNMA vial label or carton or if not stored properly.
- Do not freeze.
- Store in the original box and protect from extreme exposure to light.
- Use reconstituted product immediately or within 3 hours after reconstitution when stored at room temperature.
- Do not use if the solution in the syringe is cloudy or contains particles.
- Discard any unused reconstituted product after 3 hours.

17 PATIENT COUNSELING INFORMATION

Advise the patient:

- To read the FDA-approved patient labeling (Patient Information).
- About early signs of hypersensitivity reactions, including tachycardia, tightness of the chest, wheezing and/or acute respiratory distress, hypotension, generalized urticaria, pruritus, rhinoconjunctivitis, angioedema, lethargy, nausea, vomiting, paresthesia, and restlessness. Advise patients to discontinue use of the product if these symptoms occur and seek immediate emergency treatment with appropriate supportive care.
- To consult with their physicians or healthcare provider prior to traveling. While traveling, advise patients to bring an adequate supply of ADZYNMA based on their current regimen of treatment.

Manufactured by:
Takeda Pharmaceuticals U.S.A., Inc.
Cambridge, MA 02142
U.S. License No. 1898

ADZYNMA and are trademarks of Takeda Pharmaceuticals International AG.

BAXJECT® is a registered trademark of Baxalta Incorporated.

TAKEDA® and are registered trademarks of Takeda Pharmaceutical Company Limited.

Patented: see https://www.takeda.com/en-us/patents

©2024 Takeda Pharmaceuticals U.S.A., Inc. All rights reserved.

ADZ379 R2

Patient Information
ADZYNMA (ad-zin-muh)
(ADAMTS13, recombinant-krhn)
Lyophilized Powder for Injection, for Intravenous Use
Single-Dose Vial

Read this Patient Information before you start using ADZYNMA. This information does not take the place of talking with your healthcare provider about your medical condition or your treatment.

What is ADZYNMA?
ADZYNMA is a prescription medicine used to prevent or treat blood clots in patients with congenital thrombotic thrombocytopenic purpura (cTTP). This medicine replaces low amounts of the enzyme (ADAMTS13) in the body.

Who should not take ADZYNMA?
Do not take ADZYNMA if you have had a life-threatening allergic reaction to ADZYNMA, or any of the ingredients in ADZYNMA. See the end of this Patient Information for a complete list of ingredients in ADZYNMA.

Before you take ADZYNMA, tell your healthcare provider about all of your medical conditions, including if you:

- have any allergies, including allergies to hamsters.
- are pregnant or plan to become pregnant. It is not known if ADZYNMA will harm your unborn baby. Tell your healthcare provider right away if you become pregnant while receiving ADZYNMA.
- are breastfeeding or plan to breastfeed. It is not known if ADZYNMA passes into breast milk. Talk to your healthcare provider about the best way to feed your baby if you take ADZYNMA.

Tell your healthcare provider about all the medicines you take, including prescription medicines and over-the-counter medicines, vitamins, and herbal supplements.

How is ADZYNMA given?
ADZYNMA will be slowly injected into your vein (intravenous injection).

What are the possible side effects of ADZYNMA?
You can have an allergic reaction to ADZYNMA.
Call your healthcare provider right away and stop treatment if you get a rash or hives, itching, tightness of the throat, chest pain or tightness, difficulty breathing, lightheadedness, dizziness, nausea, or fainting.
The most common side effects that have been reported with ADZYNMA include: headache, diarrhea, migraine, abdominal pain, nausea, upper respiratory tract infection, dizziness, and vomiting.
Tell your healthcare provider about any side effect that bothers you or does not go away.
These are not all of the possible side effects of ADZYNMA. For more information, ask your healthcare provider or pharmacist.
Call your doctor for medical advice about side effects. You may report side effects to FDA at 1-800-FDA-1088.

What else should I know about ADZYNMA and hereditary ADAMTS13 deficiency (cTTP)?
Your body can form inhibitors to ADAMTS13. An inhibitor is part of the body’s normal defense system. If you form inhibitors, they may stop ADZYNMA from working properly. Consult with your healthcare provider to make sure you are carefully monitored with blood tests for the development of inhibitors to ADAMTS13.

General information about the safe and effective use of ADZYNMA
Medicines are sometimes prescribed for purposes other than those listed here. Do not use ADZYNMA for a condition for which it is not prescribed. Do not give ADZYNMA to other people, even if they have the same symptoms you have. It may harm them.

What are the ingredients in ADZYNMA?
Active ingredient: recombinant ADAMTS13.
Inactive ingredients: sodium chloride, calcium chloride dihydrate, L-histidine, mannitol, sucrose, and polysorbate 80.

Resources at Takeda available to the patients:
For more product information on ADZYNMA, please visit www.ADZYNMA.com or call 1-877-TAKEDA-7 (1-877-825-3327).
For information on additional Takeda patient resources, please visit www.ADZYNMA.com.
Manufactured by:
Takeda Pharmaceuticals U.S.A., Inc.
Cambridge, MA 02142
U.S. License No. 1898

ADZYNMA and are trademarks of Takeda Pharmaceuticals International AG.

BAXJECT® is a registered trademark of Baxalta Incorporated.

TAKEDA® and are registered trademarks of Takeda Pharmaceutical Company Limited.

Patented: see https://www.takeda.com/en-us/patents

©2024 Takeda Pharmaceuticals U.S.A., Inc. All rights reserved.

ADZ379 R2

This Patient Information has been approved by the U.S. Food and Drug Administration.

Revised 6/2024

INSTRUCTIONS FOR USE
ADZYNMA
(ad-zin-muh)
(ADAMTS13, recombinant-krhn)
Lyophilized Powder for Injection, for Intravenous Use
Single-Dose Vial
The following information is intended for medical or healthcare professionals only.

This Instructions for Use contains information on how to reconstitute and infuse ADZYNMA. This Instructions for Use is intended for the Healthcare Provider. Treatment with ADZYNMA should be prescribed and administered by a healthcare professional experienced in the treatment of blood disorders.

Important:

- For intravenous injection after reconstitution only.
- Use aseptic technique (clean and germ-free) throughout the procedure.
- Check the expiration date of the product prior to use.
- Do not use ADZYNMA if the expiration date has passed.

Storage of ADZYNMA

- Store ADZYNMA at refrigeration temperature of 36°F to 46°F [2°C to 8°C] until the expiration date stated on the carton.
- Can be stored at room temperature not to exceed 86°F/30°C for a period of 6 months, do not return to the refrigerator.
- Do not use beyond the expiration date printed on the carton or vial or if not stored properly.
- Do not freeze.
- Store vials in the original package to protect from light.

Reconstitution of ADZYNMA Using the BAXJECT II Hi-Flow Needleless Transfer Device

1. Prepare a clean, germ-free, flat surface and gather all the materials you will need for the reconstitution and infusion. Figure A depicts the materials provided in the carton box.
  Figure A
2. Do not use ADZYNMA if the expiration date has passed.
  - Use ADZYNMA within 3 hours after reconstitution and keep at room temperature not to exceed 86°F/30°C. Do not store at any other temperature. Discard any unused reconstituted product if not used within 3 hours after reconstitution.
3. Allow the vials of ADZYNMA and diluent to reach room temperature before use.
  - If the patient needs more than one vial of ADZYNMA per injection, reconstitute each vial according to the instructions stated under “Reconstitution of ADZYNMA Using the BAXJECT II Hi-Flow Needleless Transfer Device”.
  - Inspect the reconstituted ADZYNMA solution for particulate matter and discoloration prior to administration. The solution should be clear and colorless in appearance.
  - Do not administer if particulate matter or discoloration is observed.
4. Wash and dry your hands thoroughly, and put on clean exam gloves.
5. Remove plastic caps from the ADZYNMA and diluent vials and place the vials on a flat surface (Figure B).
  Figure B
6. Wipe the rubber stoppers with an alcohol swab and allow them to dry prior to use. (Figure C).
  Figure C
7. Open the BAXJECT II Hi-Flow device package by peeling away the lid, without touching the inside (Figure D).
  - Do not remove the BAXJECT II Hi-Flow device from the package.
  - Do not touch the clear plastic spike.
    Figure D
8. Turn the package with the BAXJECT II Hi-Flow device upside down and place it over the top of the diluent vial. Press straight down until the clear plastic spike pierces through the diluent vial stopper (Figure E).
  Figure E
9. Grip the BAXJECT II Hi-Flow device package at its edge and pull the package off the device (Figure F).
  - Do not remove the blue cap from the BAXJECT II Hi-Flow device.
  - Do not touch the exposed purple plastic spike.
    Figure F
10. Turn the system over so that the diluent vial is now on top. Press the BAXJECT II Hi-Flow device straight down until the purple plastic spike pierces through the ADZYNMA powder vial stopper (Figure G). The vacuum will draw the diluent into the ADZYNMA powder vial.
  - You may notice some bubbles or foam – this is normal and should soon disappear. Wait until foam or bubbles dissipate before administration.
    Figure G
11. Swirl the connected vials gently and continuously until the powder is completely dissolved (Figure H).
  - Do not shake the vial.
    Figure H
12. Visually inspect the reconstituted solution for particulate matter before administration. The solution should be clear and colorless in appearance.
  - Do not use the product if particulate matter or discoloration is observed.
13. If the dose requires more than one vial of ADZYNMA, repeat step 1 to step 12 to reconstitute each vial.
  - Use a different BAXJECT II Hi-Flow device to reconstitute each vial of ADZYNMA and diluent.

Administration of ADZYNMA

14. Take off the blue cap from the BAXJECT II Hi-Flow device (Figure I). Attach a Luer-lock syringe (Figure J).
  - Do not inject air into the system.
    Figure I
    Figure J
15. Turn the system upside down (ADZYNMA vial is now on top). Draw the reconstituted solution into the syringe by pulling the plunger back slowly (Figure K).
  - Use ADZYNMA within 3 hours after reconstitution and keep at room temperature (not to exceed 86°F/30°C). Do not store at any other temperature. Discard any unused reconstituted product if not used within 3 hours after reconstitution.
  - Do not administer ADZYNMA in the same tubing or container at the same time with other medicinal products for infusion.
    Figure K
16. If a patient is to receive more than one vial of ADZYNMA, the contents of multiple vials can be drawn into the same syringe. Repeat this process for all reconstituted vials of ADZYNMA until the total volume to be administered is reached.
17. Disconnect the syringe and attach a suitable injection needle or an infusion set.
18. Point the needle up and remove any air bubbles by gently tapping the syringe with your finger and slowly and carefully pushing air out of the syringe and needle.
19. Apply a tourniquet and clean the chosen infusion site with an alcohol swab (Figure L).
  Figure L
20. Insert the needle into the vein and remove the tourniquet.
21. Infuse the reconstituted ADZYNMA slowly, at a rate of 2 to 4 mL per minute (Figure M).
  - A syringe pump may be used to control the rate of administration.
    Figure M
22. Take the needle out of the vein, place a cotton ball or gauze on the infusion site, and apply pressure for several minutes to stop bleeding.
  - Do not recap the needle.
23. Place the needle, syringe, and empty vials in a puncture-resistant sharps container.
  - Do not dispose of syringes and needles in the regular waste.

Disposing of ADZYNMA

- Vials are for single use only. Any remaining solution in the vial must not be used and must be discarded in accordance with local requirements. Dispose used vials and other supplies in an FDA cleared sharps disposal container.
- Do not dispose of syringes and needles in the regular waste.

ADZYNMA and are trademarks of Takeda Pharmaceuticals International AG.
BAXJECT® is a registered trademark of Baxalta Incorporated.
TAKEDA® and the are registered trademarks of Takeda Pharmaceutical Company Limited.

Patented: see https://www.takeda.com/en-us/patents

Manufactured by:
Takeda Pharmaceuticals U.S.A., Inc.
Cambridge, MA 02142
U.S. License No. 1898

This Instructions for Use has been approved by the U.S. Food and Drug Administration.
Revised: 6/2024

PRINCIPAL DISPLAY PANEL - 500 IU Kit Carton

NDC 64764-140-05

Rx Only

ADZYNMA
ADAMTS13, recombinant-krhn

For Intravenous Use After Reconstitution Only

500 IU
Nominal

Single-dose vial

Dosage: See prescribing information. Prior to administration of ADZYNMA,
read the instructions for use.

Storage: Store refrigerated at 36°F to 46°F (2°C to 8°C) until the expiration date
stated on the carton, do not freeze. Can be stored at room temperature not to
exceed 86°F/30°C for a period of 6 months, do not return to refrigerator.
Store in the original carton to protect from light. See prescribing information.

Reconstitution: Use 5 mL Sterile Water for Injection, USP. Gently swirl, do not shake.
Do not refrigerate after reconstitution. Use within 3 hours of reconstitution.
Discard unused portion.

Keep out of the reach of children.

Date removed from
refrigerator and placed
at room temperature
Date _________________

PRINCIPAL DISPLAY PANEL - 1500 IU Kit Carton

NDC 64764-145-05

Rx Only

ADZYNMA
ADAMTS13, recombinant-krhn

For Intravenous Use After Reconstitution Only

1500 IU
Nominal

Single-dose vial

Dosage: See prescribing information. Prior to administration of ADZYNMA,
read the instructions for use.

Storage: Store refrigerated at 36°F to 46°F (2°C to 8°C) until the expiration date
stated on the carton, do not freeze. Can be stored at room temperature not to
exceed 86°F/30°C for a period of 6 months, do not return to refrigerator.
Store in the original carton to protect from light. See prescribing information.

Reconstitution: Use 5 mL Sterile Water for Injection, USP. Gently swirl, do not shake.
Do not refrigerate after reconstitution. Use within 3 hours of reconstitution.
Discard unused portion.

Keep out of the reach of children.

Date removed from
refrigerator and placed
at room temperature
Date _________________